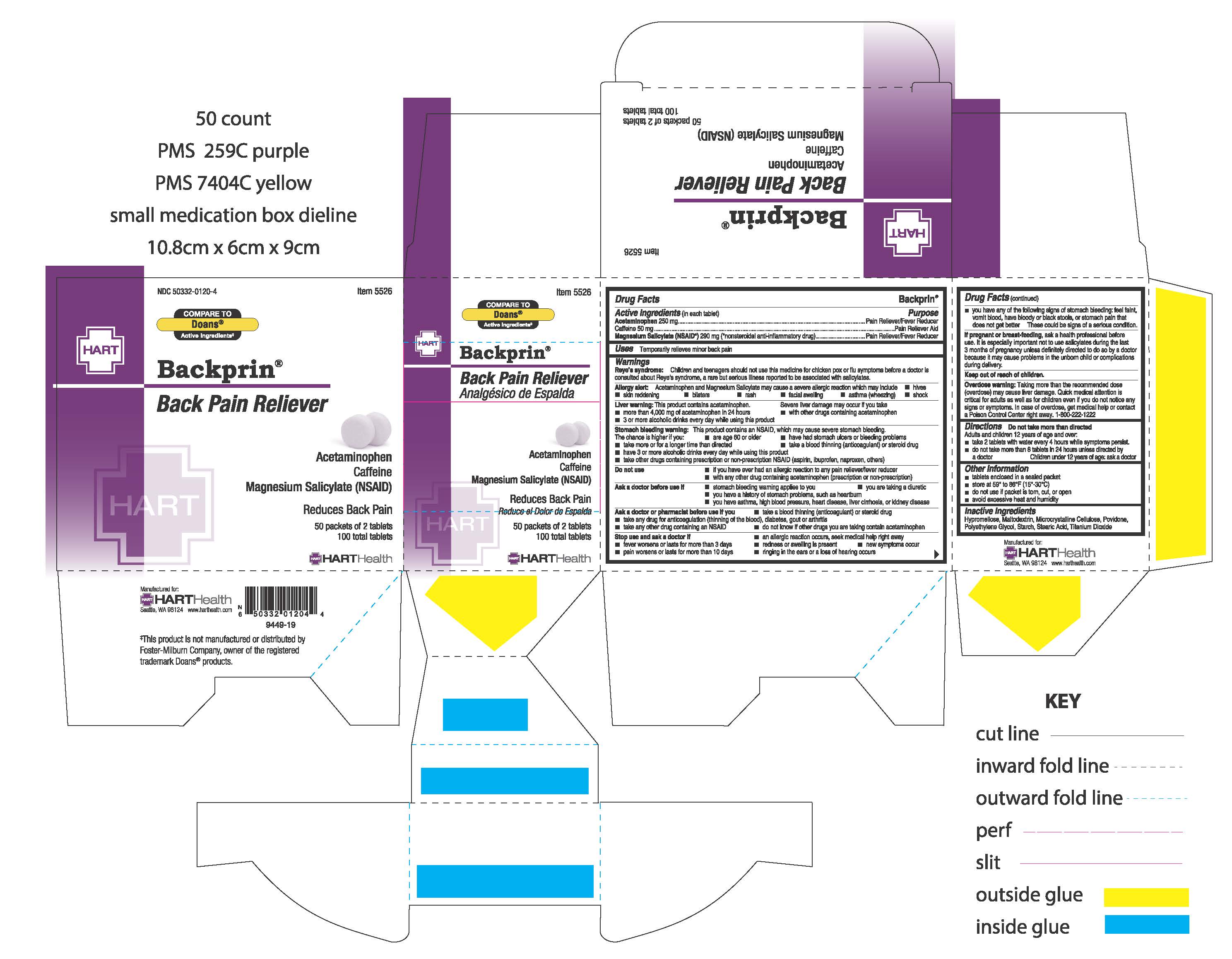 DRUG LABEL: Backprin
NDC: 50332-0116 | Form: TABLET
Manufacturer: HART Health
Category: otc | Type: HUMAN OTC DRUG LABEL
Date: 20200605

ACTIVE INGREDIENTS: ACETAMINOPHEN 250 mg/1 1; CAFFEINE 50 mg/1 1; MAGNESIUM SALICYLATE 290 mg/1 1
INACTIVE INGREDIENTS: MALTODEXTRIN; MICROCRYSTALLINE CELLULOSE; POVIDONE; STEARIC ACID; TITANIUM DIOXIDE; HYPROMELLOSES; STARCH, CORN; POLYETHYLENE GLYCOL, UNSPECIFIED

BACKPRIN

Active Ingredients (in each tablet):

Acetaminophen 250 mg

Caffeine 50 mg

Magnesium Salicylate (NSAID*) 290 mg (*nonsteroidal anti-inflammatory drug)

Purpose:

Pain Reliever/Fever Reducer

Pain Reliever Aid

Pain Reliever/Fever Reducer

Uses:

Temporarily relieves minor back pain

Warnings:

Reye's syndrome: Children and teenagers should not use this medicine for chicken pox or flu symptoms before a doctor is consulted about Reye's syndrome, a rare but serious illness reported to be associated with salicylates.

Allergy alert: Acetaminophen and Magnesium Salicylate may cause severe allergic reaction which may include hives, skin reddening, blisters, rash, facial swelling, asthma (wheezing), or shock.

Liver warning: This product contains acetaminophen. Severe liver damage may occur if you take

- more than 4,000 mg of acetaminophen in 24 hours
- with other drugs containing acetaminophen
- 3 or more alcoholic drinks every day while using this product

Stomach bleeding warning: This product contains an NSAID, which may cause severe stomach bleeding. The chance is highter if you:

- take more or for a longer time than directed
- are age 60 or older
- have had stomach ulcers or bleeding problems
- take a blood thinning (anticoagulant) or steroid drug
- have 3 or more alcoholic drinks every day while using this product
- take other drugs containing prescription or non-prescription NSAID (aspirin, ibuprofen, naproxen, others)

Do not use:

- if you have ever had an allergic reaction to any other pain reliever/fever reducer
- with any other drug containing acetaminophen (prescription or non-prescription)

Ask a doctor before use if

- you have asthma, high blood pressure, heart disease, liver cirrhosis, or kidney disease
- stomach bleeding warning applies to you
- you are taking a diuretic
- you have a history of stomach problems, such as heartburn

Ask a doctor or pharmacist before use if you

- take a blood thinning (anticoagulant) or steroid drug
- take any drug for diabetes, gout or arthritis
- do not know if other drugs you are taking contain acetaminophen
- take any other drug containing an NSAID

Stop use and ask a doctor if:

- an allergic reaction occurs, seek medical help right away
- fever worsens or lasts for more than 3 days
- redness or swelling is present
- new symptoms occur
- pain worsens or lasts for more than 10 days
- ringing in the ears or a loss of hearing occurs
- you have any of the following signs of stomach bleeding: feel faint, vomit blood, have bloods or black stools, or stomach pain that does not get better

These could be signs of a serious condition.

PREGNANCY OR BREAST FEEDING

If pregnant or breast-feeding, ask a health professional before use. It is especially important not to use salicylates during the last 3 months of pregnancy unless definitely directed to do so by a doctor because it may cause problems in the unborn child or complications during delivery.

Keep out of reach of children.

OVERDOSAGE

Overdose warning: Taking more than the recommended dose (overdose) may cause liver damage. Quick medical attention is critical for adults as well as for children even if you do not notice any signs or symtoms. In case of overdose, get medical help or contact a Poison Control Center right away. 1-800-222-1222

Directions:

Do not take more than directed

Adults and children 12 years of age and over:

- take 2 tablets with water every 4 hours while symptoms persist.
- do not take more than 8 tablets in 24 hours unless directed by a doctor

Children under 12 years of age: ask a doctor

Inactive Ingredients:

Hypromellose, Maltodextrin, Microcystalline Cellulose, Povidone, Polyethylene Glycol, Starch, Stearic Acid, Titanium Dioxide